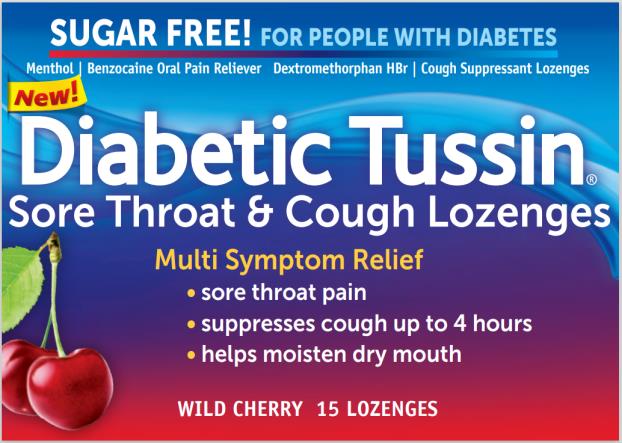 DRUG LABEL: Diabetic Tussin Sore Throat and Cough Cherry
NDC: 61787-070 | Form: LOZENGE
Manufacturer: MEDTECH PRODUCTS INC
Category: otc | Type: HUMAN OTC DRUG LABEL
Date: 20240709

ACTIVE INGREDIENTS: BENZOCAINE 6 mg/1 1; DEXTROMETHORPHAN HYDROBROMIDE 5 mg/1 1; MENTHOL 10 mg/1 1
INACTIVE INGREDIENTS: ACESULFAME POTASSIUM; FD&C BLUE NO. 1; FD&C RED NO. 40; GLYCERIN; HYDROGENATED STARCH HYDROLYSATE; SOYBEAN LECITHIN; SUCRALOSE; WATER

Diabetic Tussin Sore Throat Cherry Lozenge

Purpose

Benzocaine 6 mg......................................................... Oral pain reliever

Dextromethorphan HBr 5 mg .…………………………..Cough suppressant

Menthol 10 mg……………………………,…….………. Oral pain reliever

Uses

Temporarily relieves:

- occasional minor irritation, pain, sore throat and sore mouth
- cough due to minor throat and bronchial irritation as may occur with the common cold

Warnings

Methemoglobinemia warning:

Use of this product may cause methemoglobinemia, a serious condition that must be treated promptly because it reduces the amount of oxygen carried in blood. This can occur even if you have used this product before. Stop use and seek immediate medical attention if you or a child in your care develops:

∙ pale, gray, or blue colored skin (cyanosis)

∙ headache

∙ rapid heart rate

∙ shortness of breath

∙ dizziness or lightheadedness

∙ fatigue or lack of energy

Allergy alert: Do not use this product if you have a history of allergy to local anesthetics such as procaine, butacaine, benzocaine or other “caine” anesthetics. If a skin reaction occurs, stop use and seek medical help right away.

Sore Throat Warning: Severe or persistent sore throat, or sore throat accompanied by high fever, headache, nausea, and vomiting may be serious. Consult a doctor promptly. Do not use more than 2 days or give to children under 6 years of age unless directed by a doctor.

Do not use

- this product if you are now taking a prescription monoamine oxidase inhibitor (MAOI) (certain drugs for depression, psychiatric or emotional conditions, or Parkinson’s disease), or for 2 weeks after stopping the MAOI drug. If you are uncertain whether your prescription drug contains an MAOI, consult a health care professional before taking this product
- for teething
- In children under 6 years of age

Ask a doctor before use if you have

- a persistent or chronic cough such as occurs with smoking, asthma, or emphysema
- a cough accompanied by excessive phlegm (mucus)

When using this product

do not exceed recommended dosage.

Stop use and ask a dentist or doctor if

- sore mouth symptoms do not improve in 7 days
- irritation, pain or redness persists or worsens
- swelling, rash or fever develops
- cough persists for more than 1 week, tends to recur, or is accompanied by a fever, rash, or persistent headache. These could be signs of a serious condition.

If pregnant or breast-feeding,

ask a health professional before use.

Keep out of reach of children.

In case of overdose, get medical help or contact a Poison Control Center (1-800-222-1222) right away.

Directions

- Adults and children over 12 years of age: 2 lozenges every 4 hours – not to exceed 12 lozenges every 24 hours.
- Children 6–12 years of age: Ask a doctor before use.
- Children under 6 years of age: Do not use.

Other information

- Store between 15° - 30°C (59° - 86°F)
- Protect from moisture
- Check expiration date before using

Inactive ingredients:

acesulfame potassium, FD&C blue no. 1, FD&C red no. 40, flavor, glycerin, hydrogenated starch hydrolysate, isomalt, soy lecithin, sucralose, water

Questions?

1-800-579-8327 http://diabetictussin.com

Principal Display Panel

Diabetic Tussin® Sore Throat & Cough Lozenges

Menthol/Benzocaine Oral Pain Relievers Dextromethorphan HBr/Cough Suppressant

Wild cherry 15 lozenges